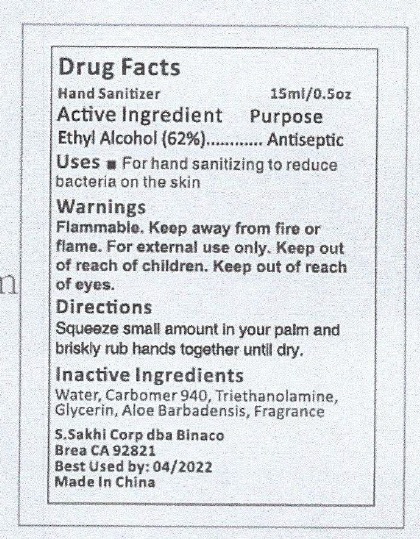 DRUG LABEL: SANITIZER
NDC: 76833-001 | Form: GEL
Manufacturer: S SAKHI CORPORATION
Category: otc | Type: HUMAN OTC DRUG LABEL
Date: 20200427

ACTIVE INGREDIENTS: ALCOHOL 6.2 mg/1 mL
INACTIVE INGREDIENTS: CARBOMER 940; WATER; ALOE VERA LEAF; GLYCERIN; TRIETHANOLAMINE BENZOATE

Hand sanitizer

Active Ingridient

Ethyl Alcohol

Purpose

Antiseptic

Use(s)

For hand sanitizing to reduce bacteria on the skin.

Warnings

For external use only.

Flammable. Keep away from fire or flame

Keep out of reach of eyes.

Directions

-Squeeze small amount in your palm and briskly rub hands together until dry.

Keep out of reach of children

Inactive Ingredient

TRIETHANOLAMINE BENZOATE,ALOE VERA LEAF,GLYCERIN,CORBOMER,WATER,FRAGRANCE